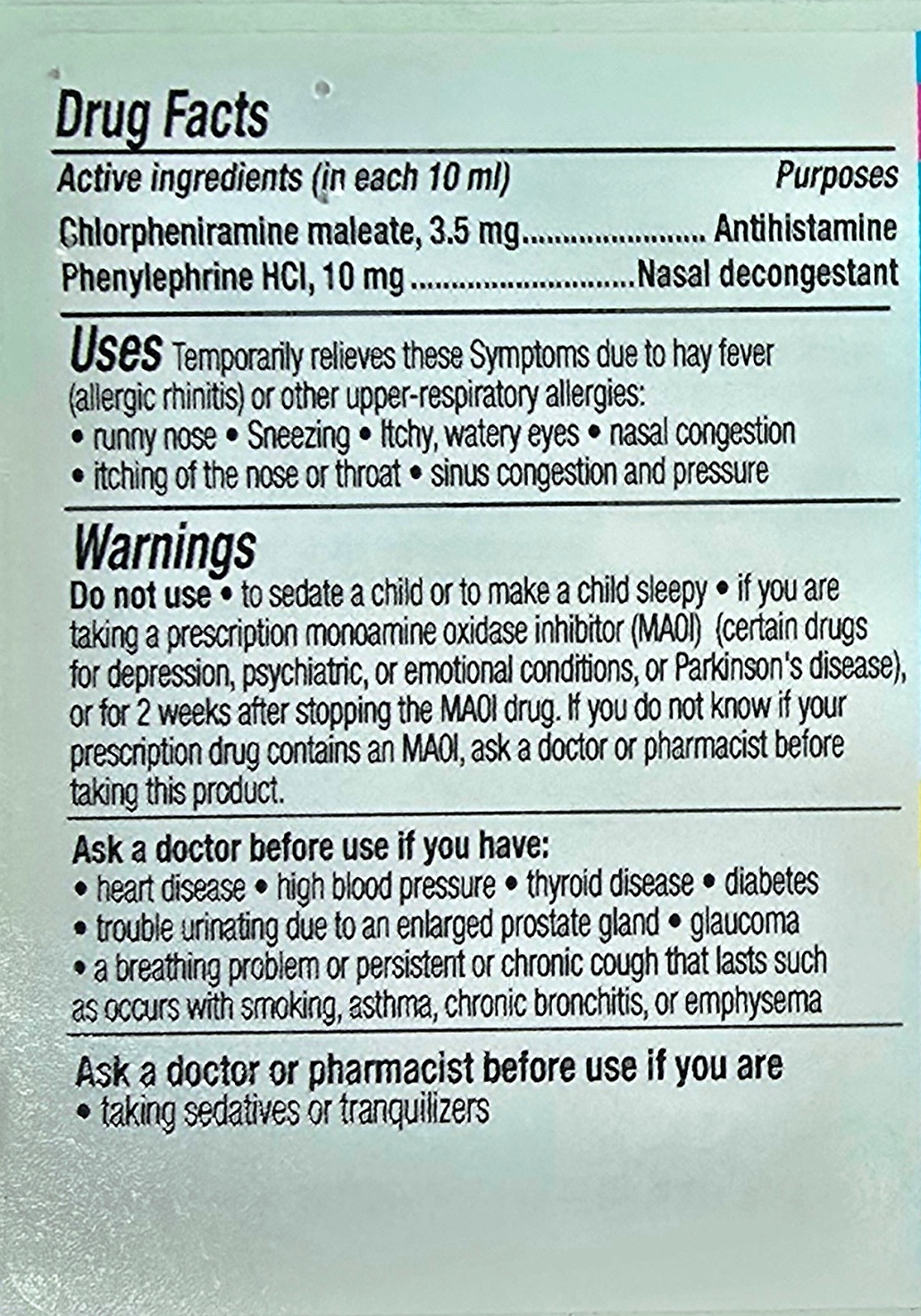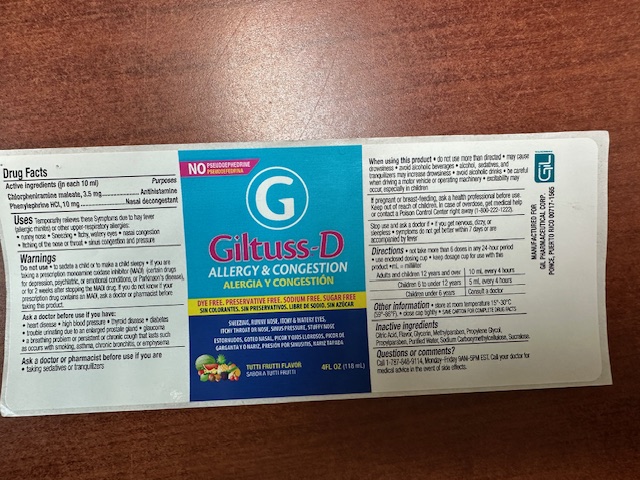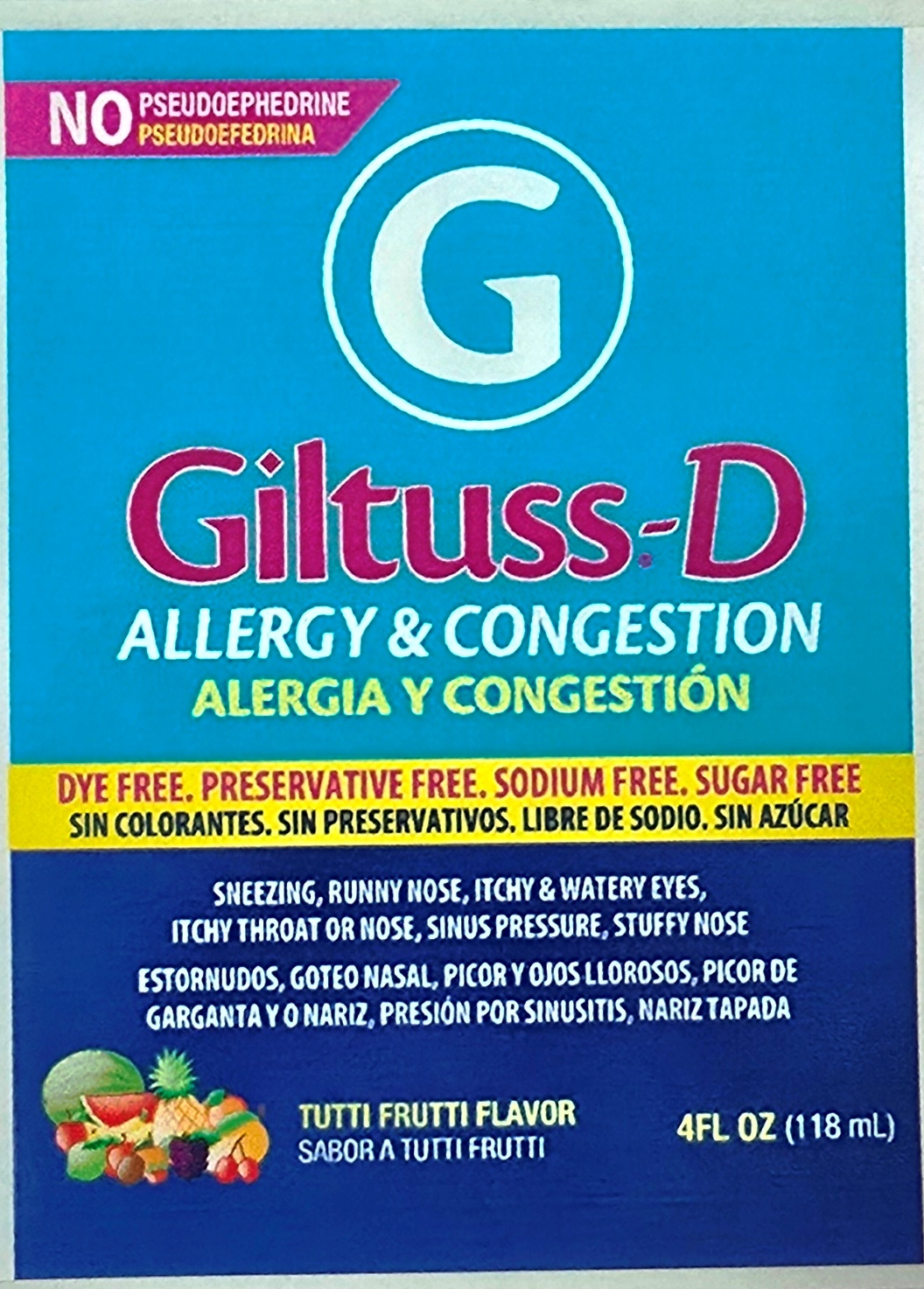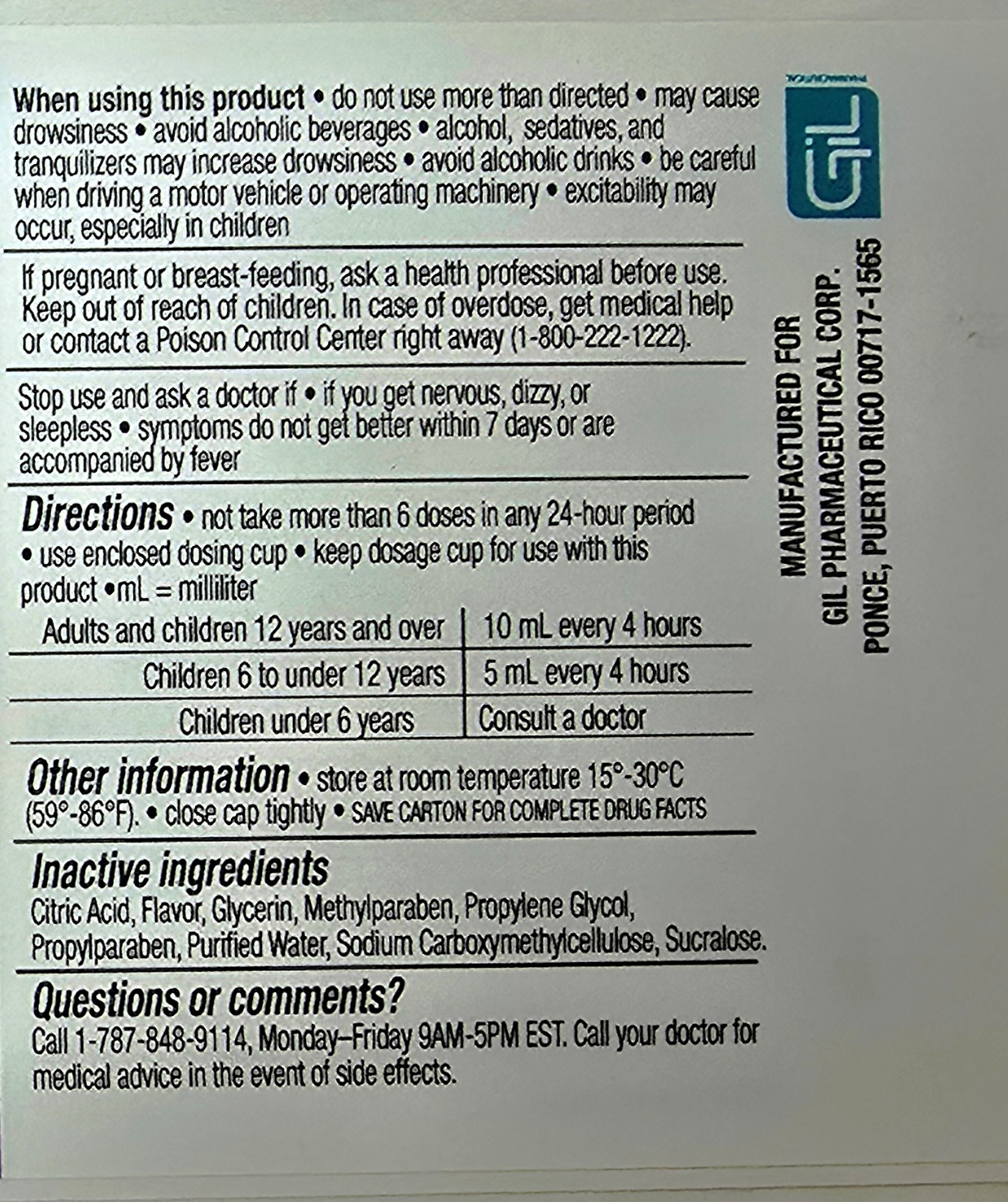 DRUG LABEL: Giltuss D
NDC: 65852-010 | Form: SYRUP
Manufacturer: Dextrum Laboratories Inc.
Category: otc | Type: HUMAN OTC DRUG LABEL
Date: 20250918

ACTIVE INGREDIENTS: PHENYLEPHRINE HYDROCHLORIDE 10 mg/10 mL; CHLORPHENIRAMINE MALEATE 3.5 mg/10 mL
INACTIVE INGREDIENTS: CITRIC ACID; METHYLPARABEN; PROPYLENE GLYCOL; SUCRALOSE; WATER; CARBOXYMETHYLCELLULOSE SODIUM; GLYCERIN; PROPYLPARABEN

Giltuss D

Purposes

Antihistamine

Nasal decongestant

Uses

Temporary relieves these symptons due to hay fever (allergy rhinitis) or other respiratory allergies:

runny nose, sneezing, itchy, watery eyes, nasal congestion, itching of nose or throat, sinus congestion and pressure

Warnings

Do not use to sedate a child or to make a child sleepy, if you ar etaking a prescription monoamine oxidase inhibitor (MAOI) (certains drugs for depression, psychiatric, or emotional conditions, or Parkinson's disease) or for 2 weeks after stopping the MAOI drug. If you do not know if your prescription drug contains an MAOI, ask a doctor or pharmacist before taking this product.

Ask a doctor before use if you have:

Heart desease, high blood pressure, thyroid desease, diabetes, trouble urinating due to enlarged prostate gland, glaucoma, a breathing problem or persistent or chronic cough that lasts such as occurs with smoking, asthma, chronic bronchitis, or ephysema

Ask a doctor or pharmacist before use if you are, taking sedatives or tranquilizers

When using

When using this product, do not use more than directed, may cause drowsiness, avoid alcoholic beverages, alcohol, sedatives, and tranquilizers may increase drowsiness, avoid alcoholic drinks, be careful when driving a motor vehicle or operating machinery, exitability may occur, especially in children.

Pregnancy or breast-feeding

If Pregnancy or breast-feeding, ask a health professional before use. Keep out of reach of children. In case or overdose, get medical help or contact a Poisson Control Center right away (1-800-222-1222)

Stop use section

Stop use and ask a doctor if, if you get nervous, dizzy or sleepless, symptons do not get better witi

hin 7 days or are accompanied by fever

ACTIVE INGREDIENT

Chlorpheniramine maleate 3.5 mg

Phenilephryne HCl, 10 mg

Directions

Directions, not take more than 6 doses in any 24 hours period, use enclosed dosing cup, keep dosage cup for use with this product, ml= mililiter

Adults and children 12 years and over 10 ml every 4 hours

Children 6 to under 12 years 5 ml every 4 hours

Children under 6 years Consult a doctor

Other information

Other information store at room temperature 15 - 30 oC (59-86 o F), close cap tightly, save carton for complete drug facts

Inactive ingredients

Citric Acid, Flavor, Glycerin, Methylparaben, Propylene Glycol, Propylparaben, Purified water, Sodium Carboxymethylcellulose, Sucralose.

Questions or Comments?

Call 1-787-848-9114 Monday-Friday 9AM-5PM EST, Call your doctor for medical advice in the event of side effects

Indication and usage section

Do not take more than 6 doses in any 24 hours period, use enclosed dosing cup, keep dosage cup for use with this product,

ml= mililiter

Adults and children 12 years and over 10 ml every 4 hours

Children 6 to under 12 years 5 ml every 4 hours

Children under 6 years Consult a doctor

Keep out of reach of children.

In case or overdose, get medical help or contact a Poison Control Center right away (1-800-222-1222)

PACKAGE LABEL

Giltuss D

Allergy & Congestion

Dye Free, preservative free, sodium free, sugar free

Sneezing, Runny Nose, Itchy & Water eyes, Itchy Throat or Nose, Sinus pressure, stuffy nose

Tutti Frutti Flavor

$ floz 118 ml